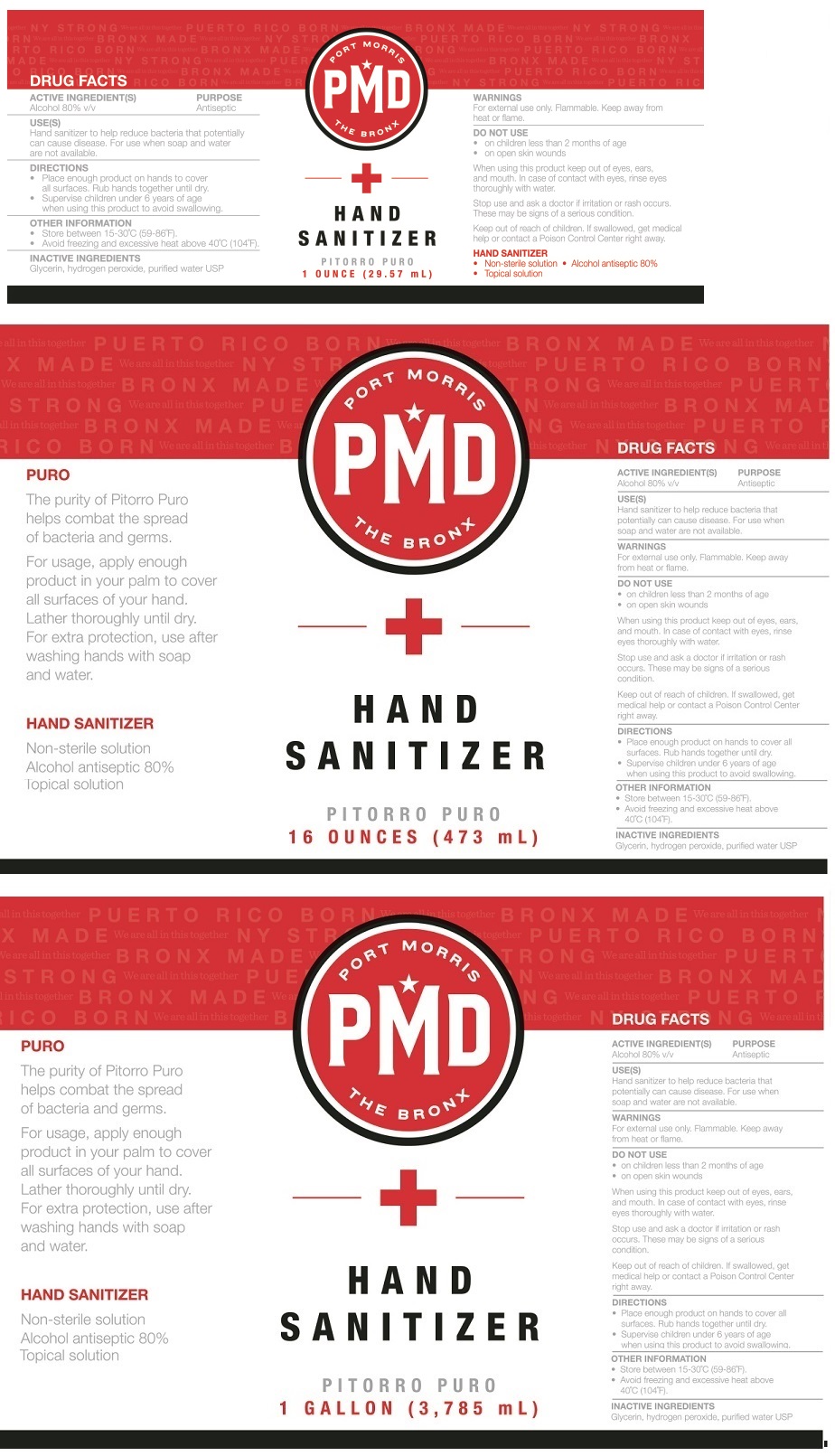 DRUG LABEL: PORT MORRIS DISTILLERY HAND SANITIZER
NDC: 77874-101 | Form: SOLUTION
Manufacturer: Pmd NY
Category: otc | Type: HUMAN OTC DRUG LABEL
Date: 20200516

ACTIVE INGREDIENTS: ALCOHOL 80 mL/100 mL
INACTIVE INGREDIENTS: GLYCERIN; HYDROGEN PEROXIDE; WATER

PORT MORRIS DISTILLERY HAND SANITIZER

ACTIVE INGREDIENT(S)

Alcohol 80% v/v

PURPOSE

Antiseptic

USE(S)

Hand sanitizer to help reduce bacteria that potentially can cause disease. For use when soap and water are not available.

WARNINGS

For external use only. Flammable. Keep away from heat or flame.

DO NOT USE

• on children less than 2 months of age

• on open skin wounds

When using this product keep out of eyes, ears, and mouth. In case of contact with eyes, rinse eyes thoroughly with water.

Stop use and ask a doctor if irritation or rash occurs. These may be signs of a serious condition.

Keep out of reach of children. If swallowed, get medical help or contact a Poison Control Center right away.

DIRECTIONS

• Place enough product on hands to cover all surfaces. Rub hands together until dry.

• Supervise children under 6 years of age when using this product to avoid swallowing.

OTHER INFORMATION

• Store between 15-30°C (59-86°F).

• Avoid freezing and excessive heat above 40°C (104°F).

INACTIVE INGREDIENTS

Glycerin, hydrogen peroxide, purified water USP

PITORRO PURO

The purity of Pitorro Puro helps combat the spread of bacteria and germs.

For usage, apply enough product in your palm to cover all surfaces of your hand.

Lather throughly until dry.

For extra protection, use after washing hands with soap and water.

Non-sterile solution

Topical solution